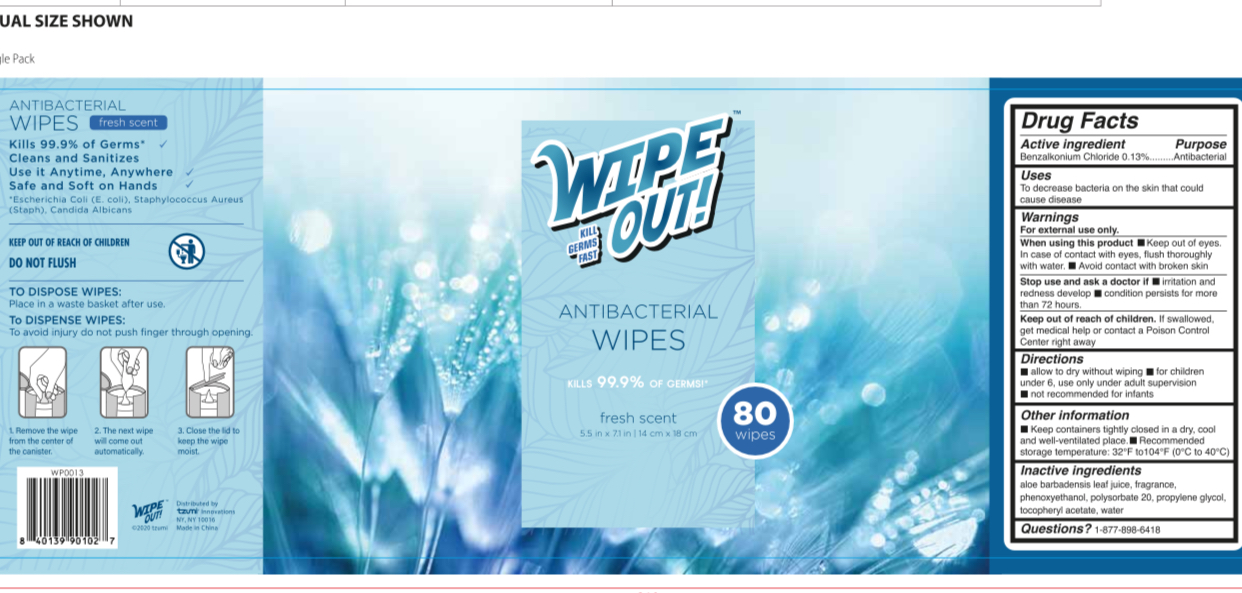 DRUG LABEL: WIPE OUT ANTIBACTERIAL WIPES fresh scent
NDC: 77878-033 | Form: SOLUTION
Manufacturer: TZUMI INNOVATIONS LLC
Category: otc | Type: HUMAN OTC DRUG LABEL
Date: 20201229

ACTIVE INGREDIENTS: BENZALKONIUM CHLORIDE 5.85 mg/1 1
INACTIVE INGREDIENTS: WATER; ALOE VERA LEAF; POLYSORBATE 20; PROPYLENE GLYCOL; PHENOXYETHANOL; .ALPHA.-TOCOPHEROL ACETATE

77878-033, Style: WP0013, Fresh scent

Active Ingredient(s)

Benzalkonium Chloride 0.13%

Purpose

Antibacterial

Use

To decrease bacteria on the skin that could cause disease

Warnings

For external use only

When using this product keep out of eyes. In case of contact with eyes, flush thoroughly with water.

Avoid contact with broken skin

Stop use and ask a doctor if irritation and redness develop, condition persists for more than 72 hours

Keep out of reach of children. If swallowed, get medical help or contact a Poison Control Center right away.

Directions

Wet hands thoroughly with product and allow to dry without wiping

For children under 6, use only under adult supervision

Not recommended for infants

Other information

- Keep containers tightly closed in a dry, cool and well ventilated place
- Recommended storage temperature: 32F to 104F (0C to 40C)

Inactive ingredients

Aloe Barbadensis Leaf Juice, Fragrance, Phenoxyethanol, Polysorbate 20, Propylene Glycol, Tocopheryl Acetate, Water